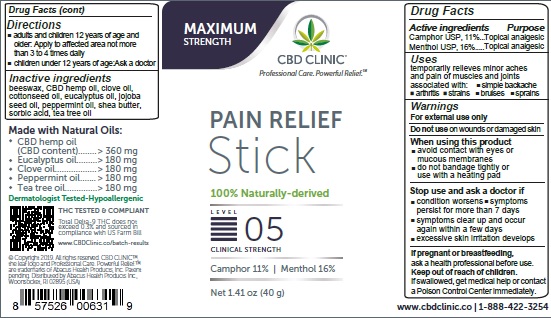 DRUG LABEL: CBD Clinic Pain Relief - Level 5
NDC: 73096-766 | Form: STICK
Manufacturer: ABACUS HEALTH PRODUCTS, INC.
Category: otc | Type: HUMAN OTC DRUG LABEL
Date: 20250407

ACTIVE INGREDIENTS: MENTHOL 16 g/100 g; CAMPHOR (NATURAL) 11 g/100 g
INACTIVE INGREDIENTS: WHITE WAX; CLOVE OIL; COTTONSEED OIL; EUCALYPTUS OIL; HEMP; JOJOBA OIL; PEPPERMINT OIL; SHEA BUTTER; SORBIC ACID; TEA TREE OIL

CBD Clinic Pain Relief - Level 5

Active Ingredients

Menthol USP, 16%, Camphor USP, 11%

Purpose

Menthol, Camphor - Topical Analgesic

Uses

temporarily relieves minor aches and pain of muscles and joints associated with:
• simple backache • arthritis • strains • bruises • sprains

Warnings

For external use only
Do not use on
• wounds or damaged skin
When using this product
• avoid contact with eyes or mucous membranes
• do not bandage tightly or use with a heating pad
Stop use and ask a doctor if
• condition worsens
• symptoms persist for more than 7 days
• symptoms clear up and occur again within a few days
• excessive skin irritation develops
If pregnant or breast-feeding
ask a health professional before use
Keep out of reach of children
If swallowed, get medical help or contact a Poison Control Center immediately

Directions

• adults and children 12 years of age and older:
apply to affected area not more than 3 to 4 times daily
• children under 12 years of age: ask a doctor

Inactive Ingredients

beeswax, CBD hemp oil, clove oil, cottonseed oil, eucalyptus oil, jojoba seed oil, peppermint oil, shea butter, sorbic acid, tea tree oil

Questions?

Call 1-888-422-3254